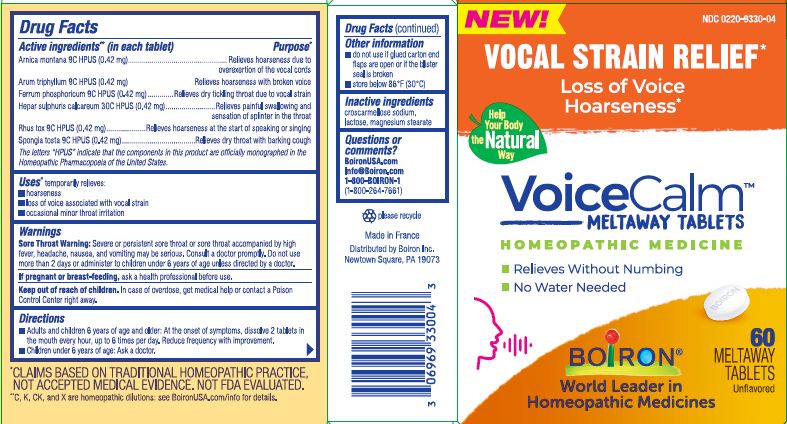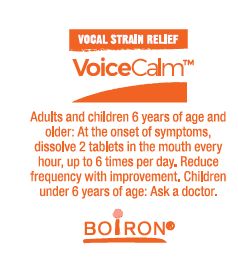 DRUG LABEL: VoiceCalm
NDC: 0220-9330 | Form: TABLET
Manufacturer: Boiron
Category: homeopathic | Type: HUMAN OTC DRUG LABEL
Date: 20260216

ACTIVE INGREDIENTS: CALCIUM SULFIDE 30 [hp_C]/1 1; TOXICODENDRON PUBESCENS LEAF 9 [hp_C]/1 1; ARNICA MONTANA WHOLE 9 [hp_C]/1 1; ARISAEMA TRIPHYLLUM ROOT 9 [hp_C]/1 1; SPONGIA OFFICINALIS SKELETON, ROASTED 9 [hp_C]/1 1; FERROSOFERRIC PHOSPHATE 9 [hp_C]/1 1
INACTIVE INGREDIENTS: LACTOSE; MAGNESIUM STEARATE; CROSCARMELLOSE SODIUM

VoiceCalm Tablets

Active ingredients** (in each tablet)

Arnica montana 9C HPUS (0.42 mg)

Arum triphyllum 9C HPUS (0.42 mg)

Ferrum phosphoricum 9C HPUS (0.42 mg)

Hepar sulphuris calcareum 30C HPUS (0.42 mg)

Rhus tox 9C HPUS (0.42 mg)

Spongia tosta 9C HPUS (0.42 mg)

The letters HPUS indicate that the components in this product are officially monographed in the Homeopathic Pharmacopoeia of the United States.

Purpose*

Arnica montana 9C HPUS (0.42 mg)……………………Relieves hoarseness due to overexertion of the vocal cords

Arum triphyllum 9C HPUS (0.42 mg)……Relieves hoarseness with broken voice

Ferrum phosphoricum 9C HPUS (0.42 mg) ……..Relieves dry tickling throat due to vocal strain

Hepar sulphuris calcareum 30C HPUS (0.42 mg)…..Relieves painful swallowing and sensation of splinter in the throat

Rhus tox 9C HPUS (0.42 mg)…………………. Relieves hoarseness at the start of speaking or singing

Spongia tosta 9C HPUS (0.42 mg)…………. Relieves dry throat with barking cough

Uses*

temporarily relieves:

- hoarseness
- loss of voice associated with vocal strain
- occasional minor throat irritation

WARNINGS

Sore Throat Warning : Severe or persistent sore throat or sore throat accompanied by high fever, headache, nausea, and vomiting may be serious. Consult a doctor promptly. Do not use more than 2 days or administer to children under 6 years of age unless directed by a doctor.

PREGNANCY OR BREAST FEEDING

If pregnant or breast-feeding, ask a health professional before use.

Keep out of reach of children. In case of overdose, get medical help or contact a Poison Control Center right away.

DOSAGE AND ADMINISTRATION

- Adults and children 6 years of age and older: At the onset of symptoms, dissolve 2 tablets in the mouth every hour, up to 6 times per day. Reduce frequency with improvement.
- Children under 6 years of age: Ask a doctor.

Other information

- do not use if glued carton end flaps are open or if blister seal is broken
- store below 86°F (30°C)

INACTIVE INGREDIENT

croscarmellose sodium, lactose, magnesium stearate

Questions or comments?

BoironUSA.com

Info@Boiron.com

1-800-BOIRON-1

(1-800-264-7661)

Made in France

Distributed by Boiron Inc.

Newtown Square, PA 19073

VOCAL STRAIN RELIEF*

Loss of Voice • Hoarseness*

60 Meltaway Tablets

- Relieves Without Numbing
- No Water Needed

*CLAIMS BASED ON TRADITIONAL HOMEOPATHIC PRACTICE, NOT ACCEPTED MEDICAL EVIDENCE. NOT FDA EVALUATED.

**C, K, CK, and X are homeopathic dilutions: see BoironUSA.com/info for details.